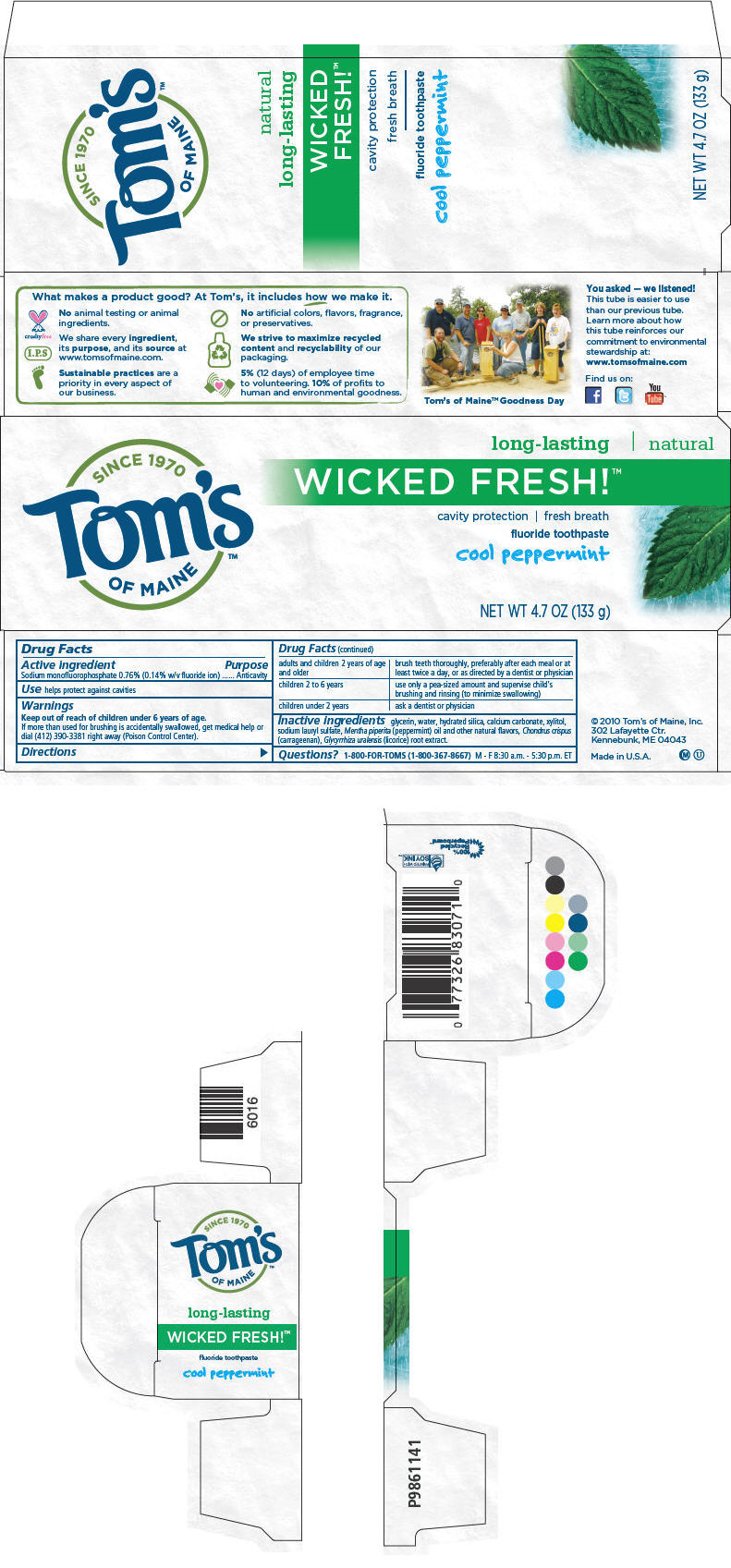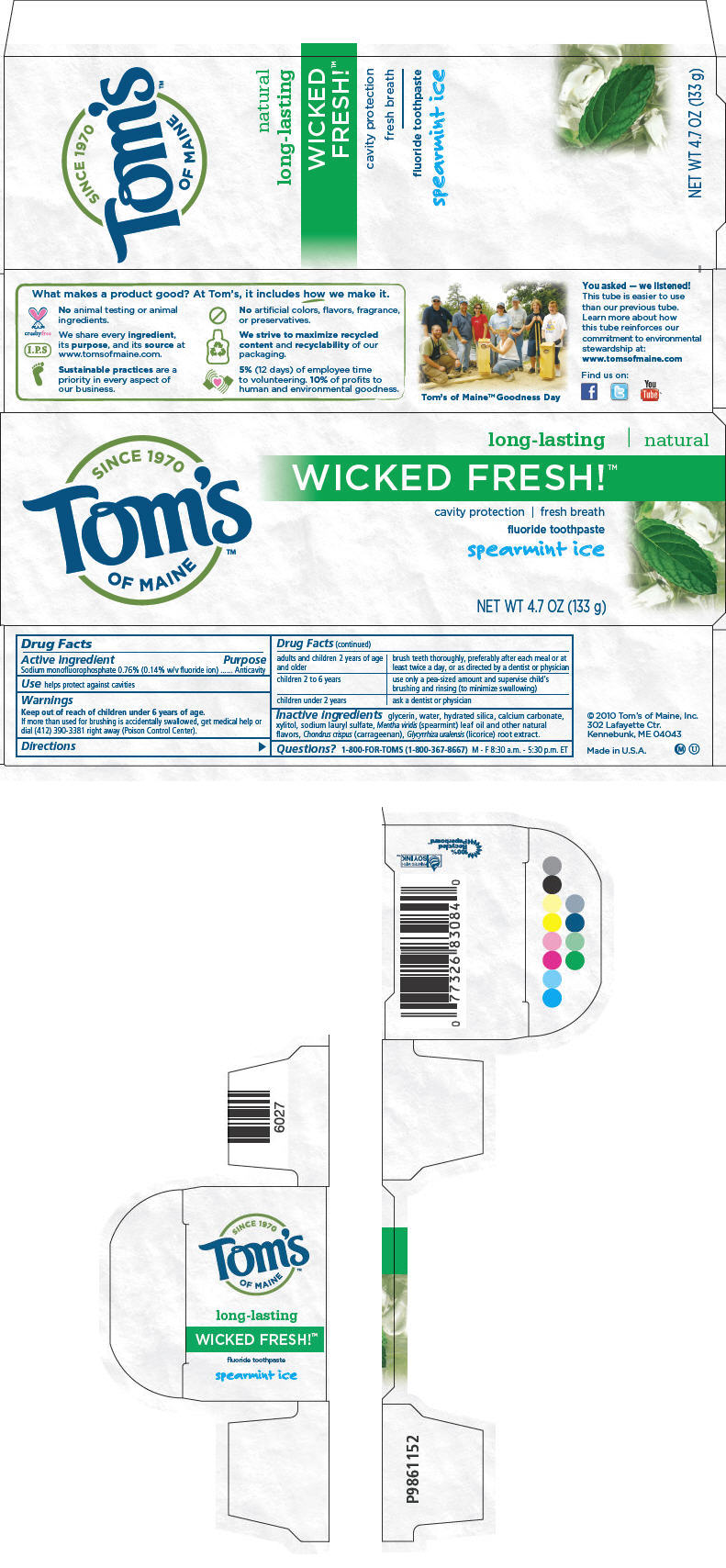 DRUG LABEL: Long-Lasting Wicked Fresh - Cool Peppermint
NDC: 51009-146 | Form: PASTE, DENTIFRICE
Manufacturer: Tom's of Maine, Inc.
Category: otc | Type: HUMAN OTC DRUG LABEL
Date: 20110509

ACTIVE INGREDIENTS: Sodium monofluorophosphate .0076 g/1 g
INACTIVE INGREDIENTS: Glycerin; Water; Calcium carbonate; Xylitol; Hydrated Silica; Carrageenan; Sodium Lauryl Sulfate

Tom's
OF MAINE™
WICKED FRESH!™
fluoride toothpaste

Drug Facts

Active ingredient

Sodium monofluorophosphate 0.76% (0.14% w/v fluoride ion)

Purpose

Anticavity

Use

helps protect against cavities

Warnings

Keep out of reach of children under 6 years of age.

If more than used for brushing is accidentally swallowed, get medical help or dial (412) 390-3381 right away (Poison Control Center).

Directions

adults and children 2 years of age and older | brush teeth thoroughly, preferably after each meal or at least twice a day, or as directed by a dentist or physician
children 2 to 6 years | use only a pea-sized amount and supervise child's brushing and rinsing (to minimize swallowing)
children under 2 years | ask a dentist or physician

Inactive ingredients

glycerin, water, hydrated silica, calcium carbonate, xylitol, sodium lauryl sulfate, Mentha piperita (peppermint) oil and other natural flavors, Chondrus crispus (carrageenan), Glycyrrhiza uralensis (licorice) root extract.

Questions?

1-800-FOR-TOMS (1-800-367-8667) M - F 8:30 a.m. - 5:30 p.m. ET

PRINCIPAL DISPLAY PANEL - 133 g Carton

SINCE 1970
Tom's
OF MAINE™

long-lasting | natural

WICKED FRESH!™

cavity protection | fresh breath

fluoride toothpaste

cool peppermint

NET WT 4.7 OZ (133 g)

PRINCIPAL DISPLAY PANEL - 133 g Carton

SINCE 1970
Tom's
OF MAINE™

long-lasting | natural

WICKED FRESH!™

cavity protection | fresh breath

fluoride toothpaste

spearmint ice

NET WT 4.7 OZ (133 g)